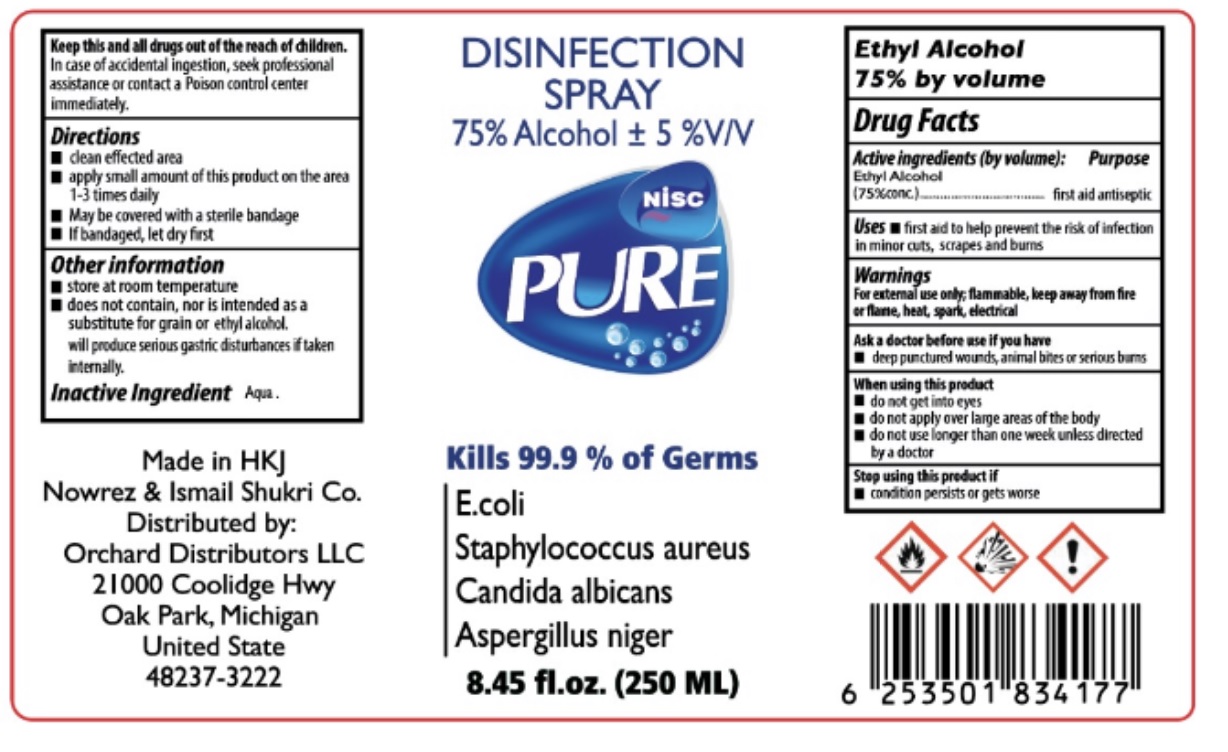 DRUG LABEL: NISC PURE DISINFECTION
NDC: 75771-235 | Form: SPRAY
Manufacturer: NOWREZ & ISMAIL SHUKRI COMPANY
Category: otc | Type: HUMAN OTC DRUG LABEL
Date: 20200706

ACTIVE INGREDIENTS: ALCOHOL 75 mL/100 mL
INACTIVE INGREDIENTS: WATER

NISC PURE DISINFECTION SPRAY

Active ingredients (by volume):

Ethyl Alcohol (75% conc.)

Purpose

first aid antiseptic

Uses

• first aid to help prevent the risk of infection in minor cuts, scrapes and burns

Warnings

For external use only; flammable, keep away from fire or flame, heat, spark, eletrical

Ask a doctor before use if you have

• deep punctured wounds, animal bites or serious burns

When using this product

• do not get into eyes

• do not apply over large areas of the body

• do not use longer than one week unless directed by a doctor

Stop using this product if

• condition persists or gets worse

KEEP OUT OF REACH OF CHILDREN

Keep this and all drugs out of reach of children. In case of accidential ingestion, seek professional assistance or contact a Poison control center immediately.

Directions

- clean effected area
- apply small amount of this product on the area 1-3 times daily
- May be covered with a sterile bandage
- If bandaged, let dry first

Other information

store at room temperature

does not contain, nor is intended as a substitute for grain or ethyl alcohol. will produce serious gastric disturbances if taken internally.

Inactive Ingredient

Aqua

Kills 99.9 % of germs

E.coli

Staphylococcus aureus

Candida albicans

Aspergillus niger

Made in HKJ

Nowrez & Ismail Shukri Co.

Distributed by:

Orchard Distributors LLC

21000 Coolidge Hwy

Oak Park, Michigan

United state

48237-3222